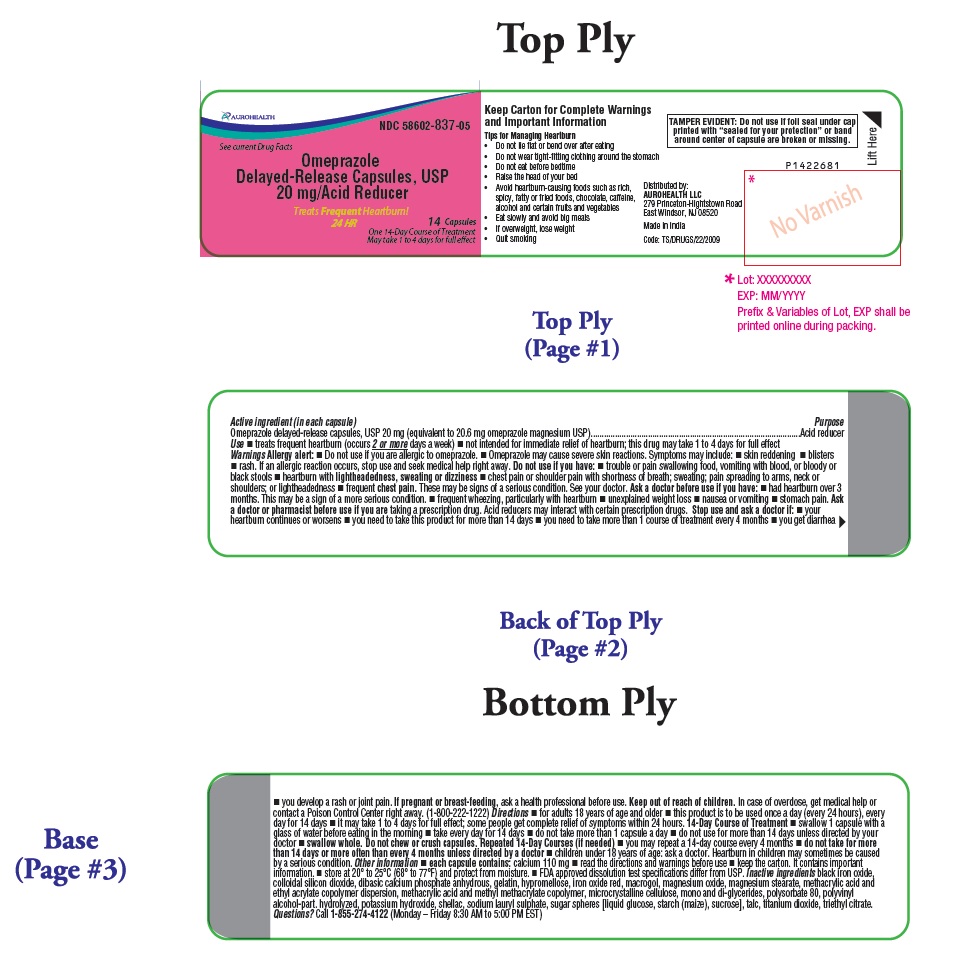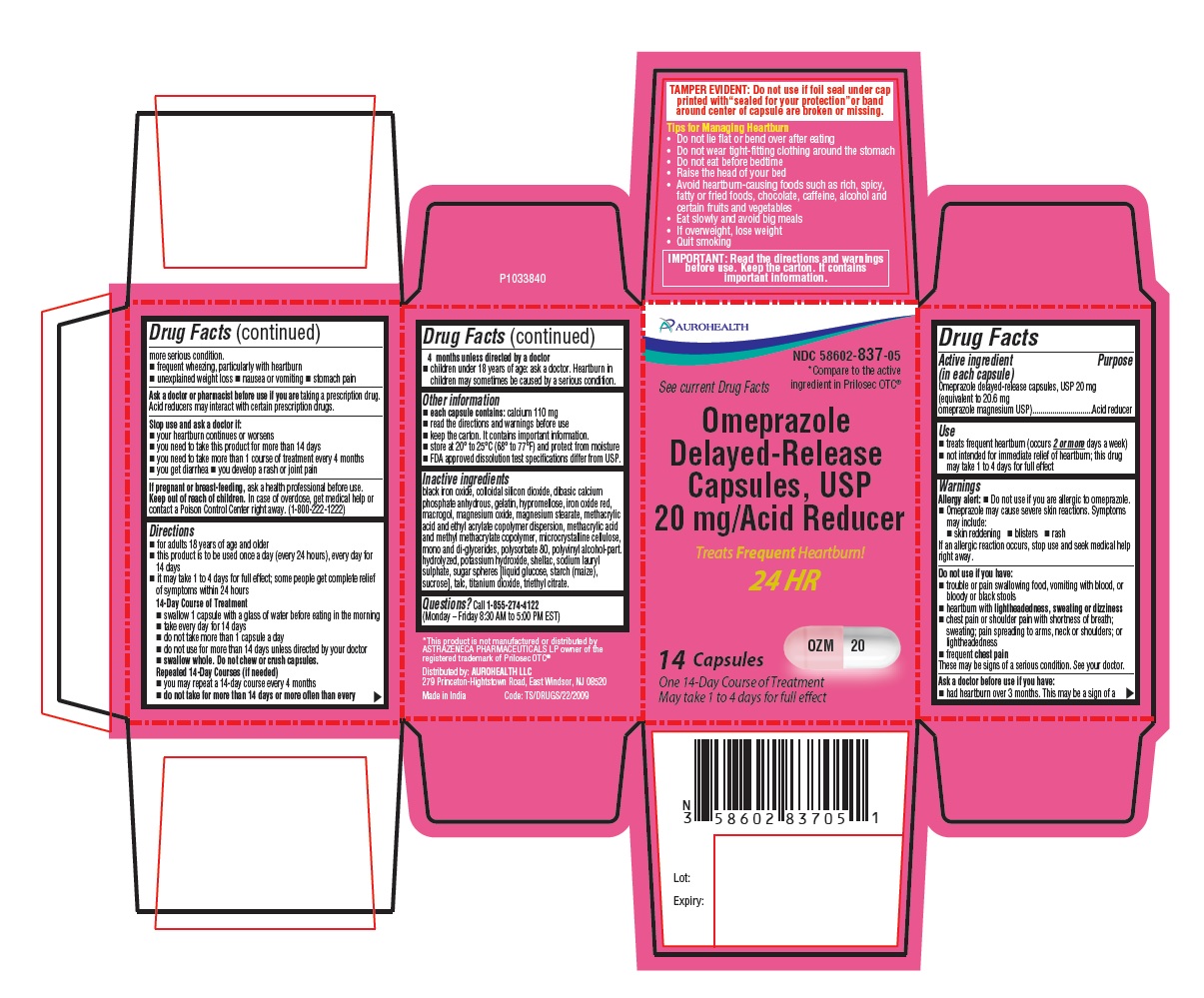 DRUG LABEL: Omeprazole
NDC: 58602-837 | Form: CAPSULE, DELAYED RELEASE
Manufacturer: Aurohealth LLC
Category: otc | Type: Human OTC Drug Label
Date: 20240219

ACTIVE INGREDIENTS: OMEPRAZOLE MAGNESIUM 20 mg/1 1
INACTIVE INGREDIENTS: FERROSOFERRIC OXIDE; SILICON DIOXIDE; ANHYDROUS DIBASIC CALCIUM PHOSPHATE; GELATIN, UNSPECIFIED; HYPROMELLOSE 2910 (3 MPA.S); FERRIC OXIDE RED; POLYETHYLENE GLYCOL 3350; MAGNESIUM OXIDE; MAGNESIUM STEARATE; METHACRYLIC ACID AND ETHYL ACRYLATE COPOLYMER; METHACRYLIC ACID - METHYL METHACRYLATE COPOLYMER (1:2); MICROCRYSTALLINE CELLULOSE 102; GLYCERYL MONO AND DIPALMITOSTEARATE; POLYSORBATE 80; POLYVINYL ALCOHOL, UNSPECIFIED; POTASSIUM HYDROXIDE; SHELLAC; SODIUM LAURYL SULFATE; DEXTROSE, UNSPECIFIED FORM; STARCH, CORN; SUCROSE; TALC; TITANIUM DIOXIDE; TRIETHYL CITRATE

Drug Facts

Active ingredient (in each capsule)

Omeprazole delayed-release capsules, USP 20 mg
(equivalent to 20.6 mg omeprazole magnesium USP)

Purpose

Acid reducer

Use

- treats frequent heartburn (occurs 2 or more days a week)
- not intended for immediate relief of heartburn; this drug may take 1 to 4 days for full effect

Warnings

Allergy alert:
• Do not use if you are allergic to omeprazole.

• Omeprazole may cause severe skin reactions. Symptoms may include:

• skin reddening • blisters • rash
If an allergic reaction occurs, stop use and seek medical help right away.

Do not use if you have:

- trouble or pain swallowing food, vomiting with blood, or bloody or black stools
- heartburn with lightheadedness, sweating or dizziness
- chest pain or shoulder pain with shortness of breath; sweating; pain spreading to arms, neck or shoulders; or lightheadedness
- frequent chest pain

These may be signs of a serious condition. See your doctor.

Ask a doctor before use if you have:

- had heartburn over 3 months. This may be a sign of a more serious condition.
- frequent wheezing, particularly with heartburn
- unexplained weight loss
- nausea or vomiting
- stomach pain

Ask a doctor or pharmacist before use if you are taking a prescription drug.

Acid reducers may interact with certain prescription drugs.

Stop use and ask a doctor if:

- your heartburn continues or worsens
- you need to take this product for more than 14 days
- you need to take more than 1 course of treatment every 4 months
- you get diarrhea
- you develop a rash or joint pain

If pregnant or breast-feeding,

ask a health professional before use.

Keep out of reach of children.

In case of overdose, get medical help or contact a Poison Control Center right away. (1-800-222-1222)

Directions

- for adults 18 years of age and older
- this product is to be used once a day (every 24 hours), every day for 14 days
- it may take 1 to 4 days for full effect; some people get complete relief of symptoms within 24 hours

14-Day Course of Treatment

- swallow 1 capsule with a glass of water before eating in the morning
- take every day for 14 days
- do not take more than 1 capsule a day
- do not use for more than 14 days unless directed by your doctor
- swallow whole. Do not chew or crush capsules.

Repeated 14-Day Courses (if needed)

- you may repeat a 14-day course every 4 months
- do not take for more than 14 days or more often than every 4 months unless directed by a doctor
- children under 18 years of age: ask a doctor. Heartburn in children may sometimes be caused by a serious condition.

Other information

- each capsule contains: calcium 110 mg
- read the directions and warnings before use
- keep the carton. It contains important information.
- store at 20° to 25°C (68° to 77°F) and protect from moisture
- FDA approved dissolution test specifications differ from USP.

Inactive ingredients

black iron oxide, colloidal silicon dioxide, dibasic calcium phosphate anhydrous, gelatin, hypromellose, iron oxide red, macrogol, magnesium oxide, magnesium stearate, methacrylic acid and ethyl acrylate copolymer dispersion, methacrylic acid and methyl methacrylate copolymer, microcrystalline cellulose, mono and di-glycerides, polysorbate 80, polyvinyl alcohol-part. hydrolyzed, potassium hydroxide, shellac, sodium lauryl sulphate, sugar spheres [liquid glucose, starch (maize), sucrose], talc, titanium dioxide, triethyl citrate.

Questions?

Call 1-855-274-4122 (Monday – Friday 8:30 AM to 5:00 PM EST)

Tips for Managing Heartburn

- Do not lie flat or bend over after eating
- Do not wear tight-fitting clothing around the stomach
- Do not eat before bedtime
- Raise the head of your bed
- Avoid heartburn-causing foods such as rich, spicy, fatty or fried foods, chocolate, caffeine, alcohol and certain fruits and vegetables
- Eat slowly and avoid big meals
- If overweight, lose weight
- Quit smoking

Distributed by:
AUROHEALTH LLC
279 Princeton-Hightstown Road
East Windsor, NJ 08520
Made in India
Code: TS/DRUGS/22/2009

PACKAGE LABEL-PRINCIPAL DISPLAY PANEL - 20 mg (14 Capsules Bottle)

AUROHEALTH
NDC 58602-837-05
See current Drug Facts
Omeprazole
Delayed-Release Capsules, USP
20 mg/Acid Reducer
Treats Frequent Heartburn!
24 HR
14 Capsules
One 14-Day Course of Treatment
May take 1 to 4 days for full effect

PACKAGE LABEL-PRINCIPAL DISPLAY PANEL - 20 mg Container Carton Label

AUROHEALTH
NDC 58602-837-05
See current Drug Facts
*Compare to the active
ingredient in Prilosec OTC®
Omeprazole
Delayed-Release
Capsules, USP
20 mg/Acid Reducer
Treats Frequent Heartburn!
24 HR
OZM 20
14 Capsules
One 14-Day Course of Treatment
May Take 1 to 4 days for full effect